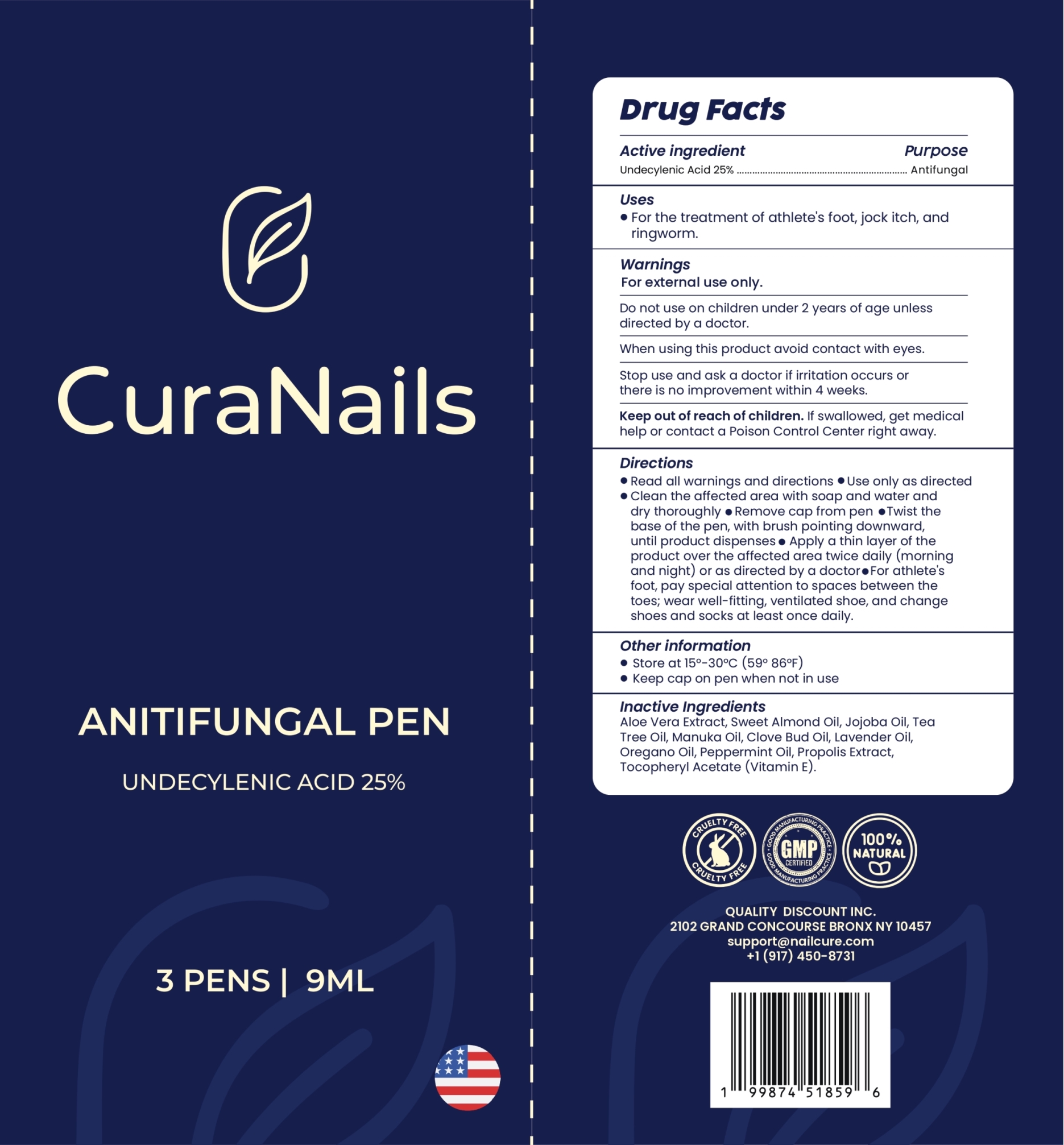 DRUG LABEL: CuraNails Antifungal Pen
NDC: 87300-001 | Form: SOLUTION
Manufacturer: Quality Discount Inc.
Category: otc | Type: HUMAN OTC DRUG LABEL
Date: 20251225

ACTIVE INGREDIENTS: UNDECYLENIC ACID 25 g/100 mL
INACTIVE INGREDIENTS: ALOE VERA LEAF; ALMOND OIL; JOJOBA OIL; TEA TREE OIL; MANUKA OIL; CLOVE OIL; LAVENDER OIL; OREGANO LEAF OIL; PEPPERMINT OIL; PROPOLIS WAX; .ALPHA.-TOCOPHEROL ACETATE

Active ingredient

Undecylenic Acid 25%

Purpose

Antifungal

Uses

For the treatment of athlete's foot, jock itch, and ringworm.

Warnings

For external use only.

Do not use on children under 2 years of age unless directed by a doctor.

When using this product avoid contact with eyes.

Stop use and ask a doctor if irritation occurs or there is no improvement within 4 weeks

Keep out of reach of children. If swallowed, get medical help or contact a Poison Control Center right away.

Directions

• Read all warnings and directions
• Use only as directed
• Clean the affected area with soap and water and dry thoroughly
• Remove cap from pen
• Twist the base of the pen, with brush pointing downward, until product dispenses
• Apply a thin layer of the product over the affected area twice daily (morning and night) or as directed by a doctor
• For athlete's foot, pay special attention to spaces between the toes; wear well-fitting, ventilated shoe, and change shoes and socks at least once daily.

Other information

• Store at 15°-30°C (59° 86°F)
• Keep cap on pen when not in use

Inactive Ingredients

Aloe Vera Extract, Sweet Almond Oil, Jojoba Oil, Tea Tree Oil, Manuka Oil, Clove Bud Oil, Lavender Oil, Oregano Oil, Peppermint Oil, Propolis Extract, Tocopheryl Acetate (Vitamin E)

Questions ?

Call +1 (917) 450-8731 or email support@nailcure.com

PACKAGE LABEL

NDC 87300-001-01